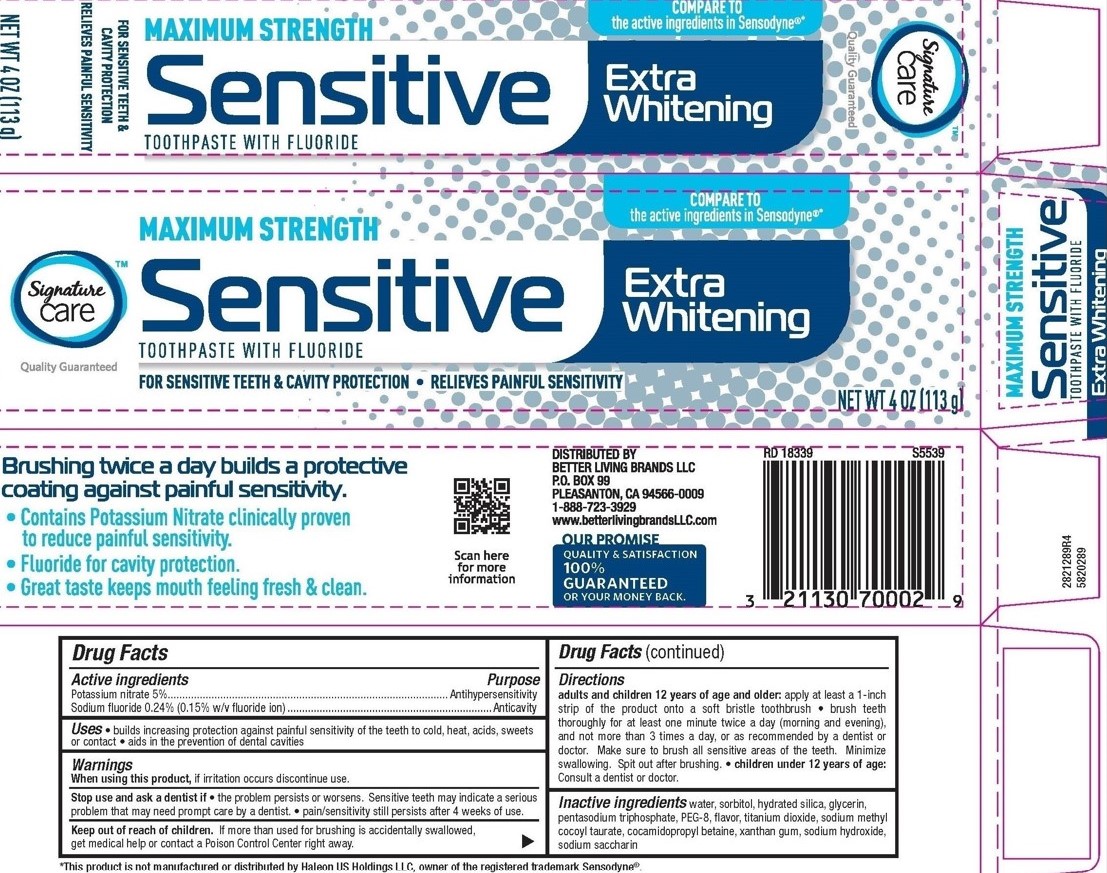 DRUG LABEL: Signature Care Sensitive
NDC: 21130-351 | Form: PASTE, DENTIFRICE
Manufacturer: Safeway
Category: otc | Type: HUMAN OTC DRUG LABEL
Date: 20251114

ACTIVE INGREDIENTS: SODIUM FLUORIDE 0.15 g/100 g; POTASSIUM NITRATE 5 g/100 g
INACTIVE INGREDIENTS: WATER; SACCHARIN SODIUM; SODIUM TRIPOLYPHOSPHATE; POLYETHYLENE GLYCOL, UNSPECIFIED; SORBITOL; TITANIUM DIOXIDE; SODIUM HYDROXIDE; GLYCERIN; XANTHAN GUM; HYDRATED SILICA; COCAMIDOPROPYL BETAINE; SODIUM METHYL COCOYL TAURATE

5820289, 5820040 Signature Care Maximum Strength Sensitive

Drug Facts

Active ingredients

Potassium nitrate 5%

Sodium fluoride 0.24% (0.15% w/v fluoride ion)

Purpose

Antihypersensitivity

Anticavity

Uses

- builds increasing protection against painful sensitivity of the teeth to cold, heat, acids, sweets or contact
- aids in the prevention of dental cavities

Warnings

When using this product do not use longer than 4 weeks unless recommended by a dentist or physician. See your dentist if the problem persists or worsens. Sensitive teeth may indicate a serious problem that may need prompt care by a dentist.

Keep out of reach of children. If more than used for brushing is accidentally swallowed, get medical help or contact a Poison Control Center right away.

Directions

Adults and children 12 years of age and older: Apply at least a 1-inch strip of the product onto a soft bristle toothbrush.

- Brush teeth thoroughly for at least one minute, preferably after each meal or at least twice a day (morning and evening), and not more than 3 times a day, or as recommended by a dentist or physican. Make sure to brush all sensitive areas of the teeth. Minimize swallowing. Spit out after brushing.
- Children under 12 years of age: consult a dentist or physician.

Other information Store in a cool, dry place. Keep tube capped when not in use.

INACTIVE INGREDIENT

Inactive ingredients cocamidopropyl betaine, flavor, glycerin, hydrated silica, PEG-8, sodium hydroxide, sodium methyl cocoyl taurate, sodium saccharin, sodium tripolyphosphate, sorbitol, titanium dioxide, water, xanthan gum

DISTRIBUTED BY BETTER LIVING BRANDS LLC, P.O. BOX 99, PLEASANTON, CA 94566-0009

1-888-723-3929 www.betterlivingbrandsLLC.com

PACKAGE LABEL

Signature Care™

MAXIMUM STRENGTH

SENSITIVE TOOTHPASTE WITH FLUORIDE

FOR SENSITIVE TEETH & CAVITY PROTECTION

RELIEVES PAINFUL SENSITIVITY

Extra Whitening

NET WT 4 OZ (113 g)